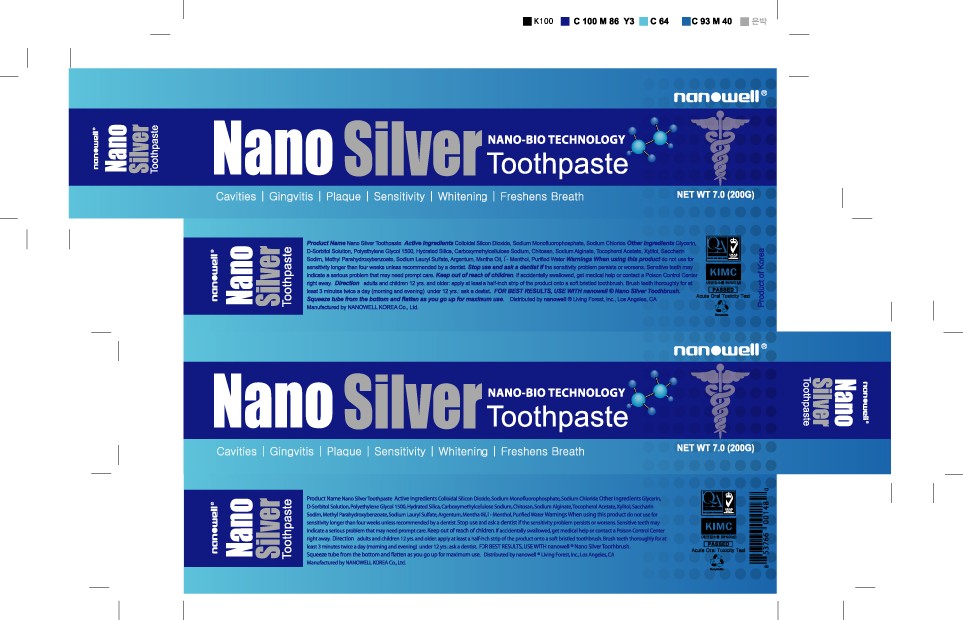 DRUG LABEL: NANO SILVER TOOTHPASTE
NDC: 45163-451 | Form: PASTE
Manufacturer: Nanowell Korea Inc
Category: otc | Type: HUMAN OTC DRUG LABEL
Date: 20100118

ACTIVE INGREDIENTS: SODIUM MONOFLUOROPHOSPHATE 1.4 g/200 g; SILICON DIOXIDE 14 g/200 g; GLYCERIN 5 g/200 g

ACTIVE INGREDIENT

Active Ingredients: Colloidal Silicon Dioxide, Sodium Monofluorophosphate, Sodium Chloride, Glycerin

INACTIVE INGREDIENT

Inactive Ingredients: D-Sorbitol Solution, Polyethylene Glycol 1500, Hydrated Silica, Carboxymethylcellulose Sodium, Chitosan, Sodium Alginate, Tocopherol Acetate, Xylitol, Saccharin Sodium, Methyl Parahydroxybenzoate, Sodium Lauryl Sulfate, Argentum, Mentha Oil, L-Menthol, Purified Water

WARNINGS

Warnings: When using this product, do not use for sensitivity longer than four weeks unless recommended by a dentist. Stop use and ask a dentist if the sensitivity problem persists or worsens. Sensitive tooth may indicate a serious problem that may need prompt care.

Keep out of reach of children. If accidentally swallowed, get medical help or contact a Poison Control Center right away.

WHEN USING

Direction: adults and children 12 yrs and older. apply at least a half-inch strip of the product onto a soft bristled toothbrush. Brush teeth thoroughly for at least 3 minutes twice a day (morning and evening). under 12 yrs ask a dentist.